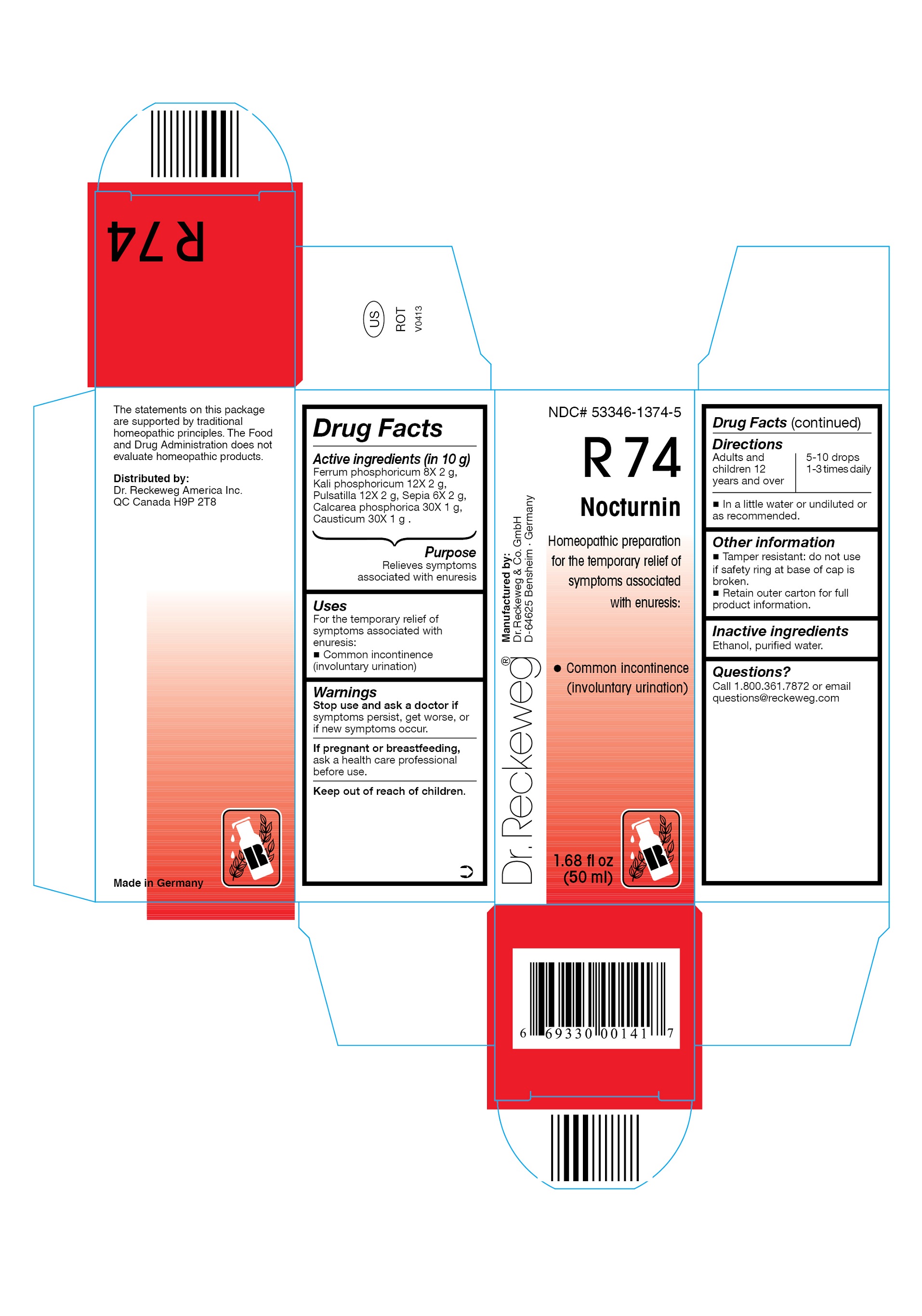 DRUG LABEL: DR. RECKEWEG R74 Nocturnin
NDC: 53346-1374 | Form: LIQUID
Manufacturer: PHARMAZEUTISCHE FABRIK DR. RECKEWEG & CO
Category: homeopathic | Type: HUMAN OTC DRUG LABEL
Date: 20130403

ACTIVE INGREDIENTS: FERRIC PHOSPHATE 8 [hp_X]/50 mL; POTASSIUM PHOSPHATE, DIBASIC 12 [hp_X]/50 mL; PULSATILLA PRATENSIS 12 [hp_X]/50 mL; SEPIA OFFICINALIS JUICE 6 [hp_X]/50 mL; CALCIUM PHOSPHATE, DIBASIC, DIHYDRATE 30 [hp_X]/50 mL; CAUSTICUM 30 [hp_X]/50 mL
INACTIVE INGREDIENTS: ALCOHOL; WATER

DR. RECKEWEG R74 Nocturnin

Active ingredients

Ferrum phosphoricum 8X 2 g, Kali phosphoricum 12X 2 g, Pulsatilla 12X 2 g, Sepia 6X 2 g, Calcarea phosphorica 30X 1 g, Causticum 30X 1 g in 10 g.

Purpose

Relieves symptoms associated with enuresis

Uses

For the temporary relief of symptoms associated with enuresis:

- Common incontinence (involuntary urination)

Warnings

Stop use and ask a doctor if symptoms persist, get worse, or if new symptoms occur.

PREGNANCY OR BREAST FEEDING

If pregnant or breastfeeding, ask a health care professional before use.

Keep out of reach of children.

Directions
Adults and children ≥ 12 years 5-10 drops 1-3 times daily in a little water or undiluted or as recommended.

Other information

- Tamper resistant: Do not use if safety ring at base of cap is broken.
- Retain outer carton for full product information.

Inactive ingredients

Ethanol, purified water.

Questions?

Call 1-800-361-7872 or email questions@reckeweg.com

PACKAGE LABEL

NDC# 53346-1374-5

Dr. Reckeweg R74 Nocturnin

Homeopathic preparation for the temporary relief of symptoms associated with enuresis:

- Common incontinence (involuntary urination)

Manufactured by:

Dr. Reckeweg Co. GmbH

D-64625 Bensheim

Germany

1.68 fl oz
(50 ml)